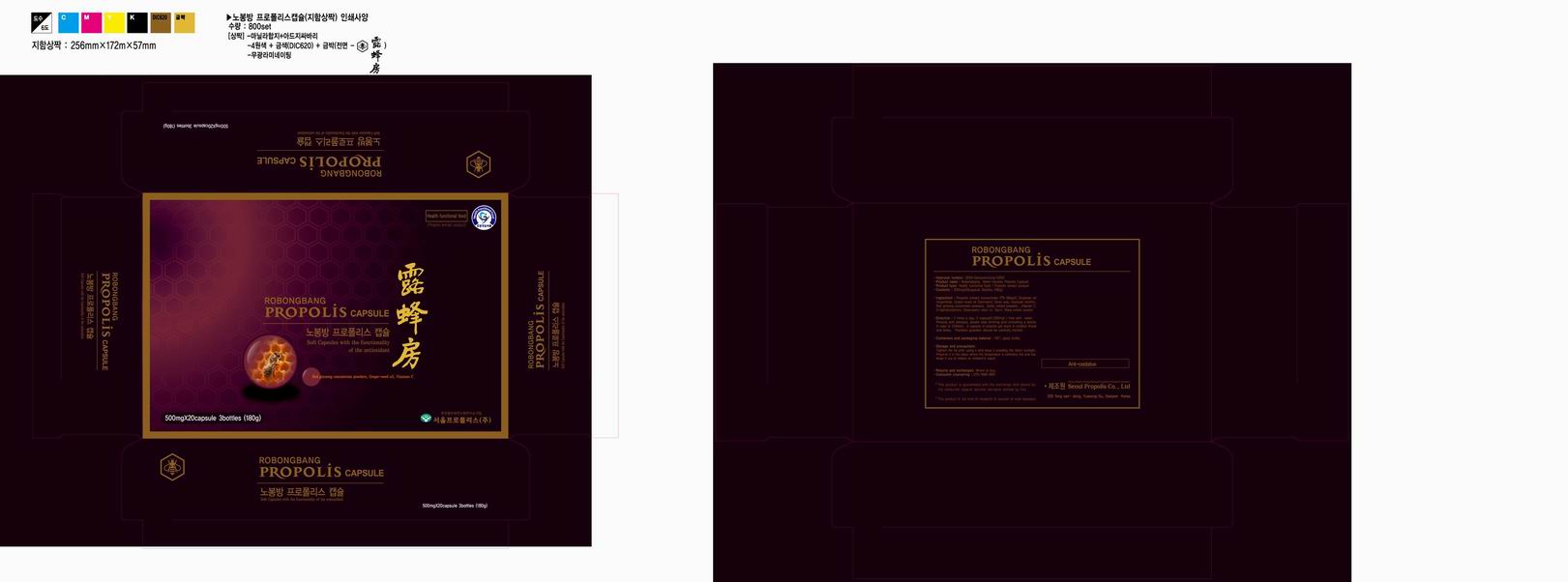 DRUG LABEL: Robongbang Propolis
NDC: 76254-2001 | Form: CAPSULE
Manufacturer: Seoul Propolis
Category: otc | Type: HUMAN OTC DRUG LABEL
Date: 20171228

ACTIVE INGREDIENTS: PROPOLIS WAX 85 mg/1 1
INACTIVE INGREDIENTS: SOYBEAN; VITIS VINIFERA SEED; WHITE WAX; LECITHIN, SOYBEAN; PANAX GINSENG ROOT WATER; GARLIC; ASCORBIC ACID; .ALPHA.-TOCOPHEROL ACETATE, D-; 1-OCTACOSANOL; TAURINE

Drug Facts

ACTIVE INGREDIENT

propolis

inactive ingredient: soybean oil, grape seed oil, wax, soybean lecithin, red ginseng concentrate powders, garlic extract powders, vitamin C, d-alphatocopherol, octacosanol retain oil, taurin, maca extract

PURPOSE

anti oxidant for the health
energizing for the life
health maintenance and improvement
to reduce the excessive stress

keep out of reach of the children

INDICATIONS AND USAGE

take 2 capsules twice a day with water

WARNINGS

keep in a cool place
avode direct sunlight

DOSAGE AND ADMINISTRATION

for oral use only